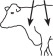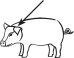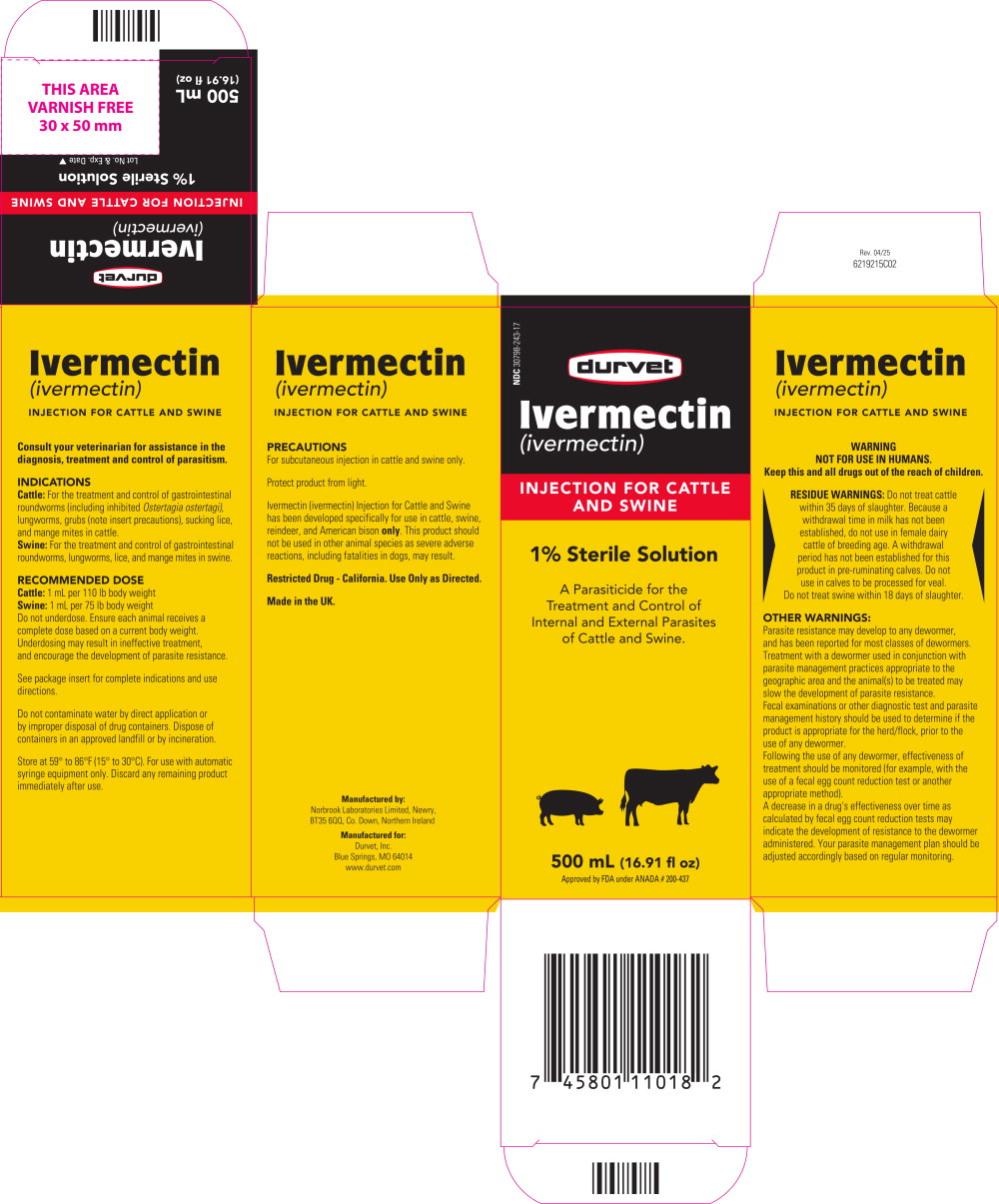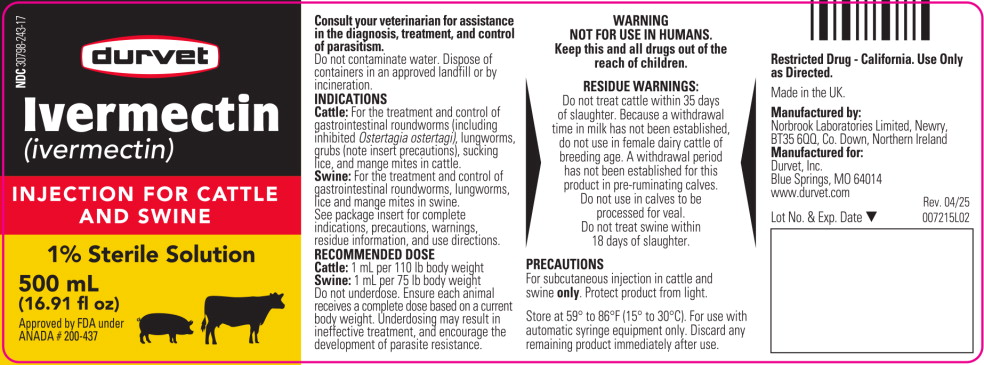 DRUG LABEL: Ivermectin for Cattle and Swine
NDC: 30798-243 | Form: INJECTION, SOLUTION
Manufacturer: Durvet, Inc.
Category: animal | Type: OTC ANIMAL DRUG LABEL
Date: 20251107

ACTIVE INGREDIENTS: ivermectin 10 mg/1 mL
INACTIVE INGREDIENTS: propylene glycol

Durvet
Ivermectin
(ivermectin)

INJECTION FOR CATTLE AND SWINE

1% Sterile Solution

A Parasiticide for the Treatment and Control of Internal and External Parasites of Cattle and Swine.

Consult your veterinarian for assistance in the diagnosis, treatment and control of parasitism.

INTRODUCTION

Ivermectin (ivermectin) Injection is an injectable parasiticide for cattle and swine. One low-volume dose effectively treats and controls the following internal and external parasites that may impair the health of cattle and swine: gastrointestinal roundworms (including inhibited Ostertagia ostertagi in cattle), lungworms, grubs, sucking lice, and mange mites of cattle; and gastrointestinal roundworms, lungworms, lice, and mange mites of swine. Ivermectin's convenience, broad-spectrum efficacy and safety margin make Ivermectin Injection a unique product for parasite control of cattle and swine.

PRODUCT DESCRIPTION

Ivermectin is derived from the avermectins, a family of potent, broad-spectrum antiparasitic agents isolated from fermentation of Streptomyces avermitilis.

Ivermectin Injection is a clear, ready-to-use, sterile solution containing 1% ivermectin, 40% glycerol formal, and propylene glycol q.s. ad 100%. Ivermectin Injection is formulated to deliver the recommended dose level of 200 mcg ivermectin/kilogram of body weight in cattle when given subcutaneously at the rate of 1 mL/110 lb (50 kg). In Swine, Ivermectin Injection is formulated to deliver the recommended dose level of 300 mcg ivermectin/kilogram body weight when given subcutaneously in the neck at the rate of 1 mL per 75 lb (33 kg).

MODE OF ACTION

Ivermectin is a member of the macrocyclic lactone class of endectocides which have a unique mode of action. Compounds of the class bind selectively and with high affinity to glutamate-gated chloride ion channels which occur in invertebrate nerve and muscle cells. This leads to an increase in the permeability of the cell membrane to chloride ions with hyperpolarization of the nerve or muscle cell, resulting in paralysis and death of the parasite. Compounds of this class may also interact with other ligand-gated chloride channels, such as those gated by the neurotransmitter gamma-aminobutyric acid (GABA).

The margin of safety for compounds of this class is attributable to the fact that mammals do not have glutamate-gated chloride channels, the macrocyclic lactones have a low affinity for other mammalian ligand-gated chloride channels and they do not readily cross the blood-brain barrier.

INDICATIONS

Cattle: Ivermectin Injection is indicated for the effective treatment and control of the following harmful species of gastrointestinal roundworms, lungworms, grubs, sucking lice, and mange mites in cattle:

Gastrointestinal Roundworms (adults and fourth-stage larvae):

Ostertagia ostertagi (including inhibited O. ostertagi)

O. lyrata

Haemonchus placei

Trichostrongylus axei

T. colubriformis

Cooperia oncophora

C. punctata

C. pectinata

Oesophagostomum radiatum

Bunostomum phlebotomum

Nematodirus helvetianus (adults only)

N. spathiger (adults only)

Lungworms (adults and fourth-stage larvae):

Dictyocauius viviparus

Cattle Grubs (parasitic stages):

Hypoderma bovis

H. lineatum

Sucking Lice:

Linognathus vituli

Haematopinus eurysternus

Solenopotes capillatus

Mites (scabies):

Psoroptes ovis (syn. P communis var. bovis)

Sarcoptes scabiei var. bovis

Persistent Activity

Ivermectin injection has been proved to effectively control infections and to protect cattle from reinfection with Dictyocaulus viviparus and Oesophagostomum radiatum for 28 days after treatment; Ostertagia ostertagi, Trichostrongylus axei and Cooperia punctata for 21 days after treatment; Haemonchus placei and Cooperia oncophora for 14 days after treatment.

Swine: Ivermectin Injection is indicated for the effective treatment and control of the following harmful species of gastrointestinal roundworms, lungworms, lice, and mange mites in swine:

Gastrointestinal Roundworms:

Large roundworm, Ascaris suum

(adults and fourth-stage larvae)

Red stomach worm, Hyostrongylus rubidus

(adults and fourth-stage larvae)

Nodular worm, Oesophagostomum spp.

(adults and fourth-stage larvae)

Threadworm, Strongyloides ransomi (adults)

Somatic Roundworm Larvae:

Threadworm, Strongyloides ransomi (somatic larvae)

Sows must be treated at least seven days before farrowing to prevent infection in piglets.

Lungworms:

Metastrongylus spp. (adults)

Lice:

Haematopinus suis

Mange Mites:

Sarcoptes scabiei var. suis

DOSAGE

Cattle: Ivermectin Injection should be given only by subcutaneous injection under the loose skin in front of or behind the shoulder at the recommended dose level of 200 mcg of ivermectin per kilogram of body weight. Each mL of Ivermectin Injection contains 10 mg of ivermectin, sufficient to treat 110 lb (50 kg) of body weight (maximum 10 mL per injection site).

Body Weight (lb) | Dose Volume (mL)
220 | 2
330 | 3
440 | 4
550 | 5
660 | 6
770 | 7
880 | 8
990 | 9
1100 | 10

Swine: Ivermectin Injection should be given only by subcutaneous injection in the neck of swine at the recommended dose level of 300 mcg of ivermectin per kilogram (2.2 lb) of body weight. Each mL of Ivermectin Injection contains 10 mg of ivermectin, sufficient to treat 75 lb of body weight.

 | Body Weight (lb) | Dose Volume (mL)
Growing Pigs | 19 38 75 150 | ¼ ½ 1 2
Breeding Animals | 225 | 3
(Sows, Gilts, and Boars) | 300 | 4
 | 375 | 5
 | 450 | 6

Do not underdose. Ensure each animal receives a complete dose based on a current body weight. Underdosing may result in ineffective treatment, and encourage the development of parasite resistance.

ADMINISTRATION

Cattle: Ivermectin Injection is to be given subcutaneously only, to reduce risk of potentially fatal clostridial infection of the injection site.

Animals should be appropriately restrained to achieve the proper route of administration. Use of a 16-gauge, 1/2 to 3/4 inch needle is suggested.

Inject under the loose skin in front of or behind the shoulder (see illustration).

Any single-dose syringe or standard automatic syringe equipment may be used with the 50 mL or 100 mL pack size. When using the 250, 500, or 1000 mL pack size, use only automatic syringe equipment.

Use sterile equipment and sanitize the injection site by applying a suitable disinfectant. Clean, properly disinfected needles should be used to reduce the potential for injection site infections.

No special handling or protective clothing is necessary,

Swine: Ivermectin (ivermectin) Injection is to be given subcutaneously in the neck. Animals should be appropriately restrained to achieve the proper route of administration. Use of a 16- or 18-gauge needle is suggested for sows and boars, while an 18- or 20-gauge needle may be appropriate for young animals. Inject under the skin, immediately behind the ear (see illustration).

When using the 100, 250, 500 or 1000 mL pack size, use only automatic syringe equipment. As with any injection, sterile equipment should be used. The injection site should be cleaned and disinfected with alcohol before injection. The rubber stopper should also be disinfected with alcohol to prevent contamination of the contents. Mild and transient pain reactions may be seen in some swine following subcutaneous administration.

Recommended Treatment Program

Swine: At the time of initiating any parasite control program, it is important to treat all breeding animals in the herd. After the initial treatment, use Ivermectin Injection regularly as follows:

BREEDING ANIMALS

Sows: | Treat prior to farrowing, preferably 7-14 days before, to minimize infection of piglets.
Gilts: | Treat 7-14 days prior to breeding.
 | Treat 7-14 days prior to farrowing.
Boars: | Frequency and need for treatments are dependent upon exposure.
 | Treat at least two times a year.

FEEDER PIGS

(Weaners/Growers/Finishers)

All weaner/feeder pigs should be treated before placement in clean quarters. Pigs exposed to contaminated soil or pasture may need retreatment if reinfection occurs.

NOTE:

(1) Ivermectin Injection has a persistent drug level sufficient to control mite infestations throughout the egg to adult life cycle. However, since the ivermectin effect is not immediate, care must be taken to prevent reinfestation from exposure to untreated animals or contaminated facilities. Generally, pigs should not be moved to clean quarters or exposed to uninfested pigs for approximately one week after treatment. Sows should be treated at least one week before farrowing to minimize transfer of mites to newborn baby pigs.
(2) Louse eggs are unaffected by Ivermectin Injection and may require up to three weeks to hatch. Louse infestations developing from hatching eggs may require retreatment.
(3) Consult a veterinarian for aid in the diagnosis and control of internal and external parasites of swine.

Special Minor Use

Reindeer: For the treatment and control of warbles (Oedemagena tarandi) in reindeer, inject 200 micrograms ivermectin per kilogram of body weight, subcutaneously. Follow use directions for cattle as described under ADMINISTRATION.

American Bison: For the treatment and control of grubs (Hypoderma bovis) in American bison, inject 200 micrograms ivermectin per kilogram of body weight, subcutaneously. Follow use directions for cattle as described under ADMINISTRATION.

RESIDUE WARNINGS: Do not treat reindeer or American bison within 8 weeks (56 days) of slaughter.

WARNING

NOT FOR USE IN HUMANS.

Keep this and all drugs out of the reach of children.

The Safety Data Sheet (SDS) contains more detailed occupational safety information. To report suspected adverse drug events, for technical assistance, or to obtain a copy of the SDS, contact Norbrook, Inc at 1-866-591-5777. For additional information about adverse drug experience reporting for animal drugs, contact FDA at 1 -888-FDA-VETS or http://www.fda.gov/reportanimalae.

RESIDUE WARNINGS: Do not treat cattle within 35 days of slaughter. Because a withdrawal time in milk has not been established, do not use in female dairy cattle of breeding age. A withdrawal period has not been established for this product in pre-ruminating calves.
Do not use in calves to be processed for veal.
Do not treat swine within 18 days of slaughter.

PRECAUTIONS

Transitory discomfort has been observed in some cattle following subcutaneous administration. A low incidence of soft tissue swelling at the injection site has been observed. These reactions have disappeared without treatment. For cattle, divide doses greater than 10 mL between two injection sites to reduce occasional discomfort or site reaction.

Use sterile equipment and sanitize the injection site by applying a suitable disinfectant. Clean, properly disinfected needles should be used to reduce the potential for injection site infections.

Observe cattle for injection site reactions. Reactions may be due to clostridial infection and should be aggressively treated with appropriate antibiotics. If injection site infections are suspected, consult your veterinarian.

This product is not for intravenous or intramuscular use.

Protect product from light.

Ivermectin Injection for Cattle and Swine has been developed specifically for use in cattle, swine, reindeer, and American bison only. This product should not be used in other animal species as severe adverse reactions, including fatalities in dogs, may result.

When to Treat Cattle with Grubs

Ivermectin Injection effectively controls all stages of cattle grubs. However, proper timing of treatment is important. For most effective results, cattle should be treated as soon as possible after the end of the heel fly (warble fly) season. Destruction of Hypoderma larvae (cattle grubs) at the period when these grubs are in vital areas may cause undesirable host-parasite reactions including the possibility of fatalities. Killing Hypoderma Iineatum when it is in the tissue surrounding the esophagus (gullet) may cause salivation and bloat; killing H. bovis when it is in the vertebral canal may cause staggering or paralysis. These reactions are not specific to treatment with Ivermectin Injection, but can occur with any successful treatment of grubs. Cattle should be treated either before or after these stages of grub development. Consult your veterinarian concerning the proper time for treatment.

Cattle treated with Ivermectin Injection after the end of the heel fly season may be retreated with Ivermectin Injection during the winter for internal parasites, mange mites, or sucking lice without danger of grub-related reactions. A planned parasite control program is recommended.

OTHER WARNINGS:

Parasite resistance may develop to any dewormer, and has been reported for most classes of dewormers.

Treatment with a dewormer used in conjunction with parasite management practices appropriate to the geographic area and the animal(s) to be treated may slow the development of parasite resistance.

Fecal examinations or other diagnostic test and parasite management history should be used to determine if the product is appropriate for the herd/flock, prior to the use of any dewormer. Following the use of any dewormer, effectiveness of treatment should be monitored (for example, with the use of a fecal egg count reduction test or another appropriate method).

A decrease in a drug's effectiveness over time as calculated by fecal egg count reduction tests may indicate the development of resistance to the dewormer administered. Your parasite management plan should be adjusted accordingly based on regular monitoring.

STORAGE

Store at 59° to 86°F (15° to 30°C). Use within 60 days of first puncture and puncture a maximum of 25 times. If more than 25 punctures are anticipated, the use of multi-dosing equipment is recommended. When using a draw-off spike or needle with bore diameter larger than 16 gauge, discard any remaining product immediately after use. For 500 mL, and 1000 mL sizes: For use with automatic syringe equipment only. Discard any remaining product immediately after use.

ENVIRONMENTAL SAFETY

Studies indicate that when ivermectin comes in contact with soil, it readily and tightly binds to the soil and becomes inactive over time. Free ivermectin may adversely affect fish and certain aquatic organisms. Do not permit water runoff from feedlots to enter lakes, streams, or ponds. Do not contaminate water by direct application or by improper disposal of drug containers. Dispose of containers in an approved landfill or by incineration.

As with other avermectins, ivermectin is excreted in the dung of treated animals and can inhibit the reproduction and growth of pest and beneficial insects that use dung as a source of food and for reproduction. The magnitude and duration of such effects are species and life-cycle specific. When used according to label directions, the product is not expected to have an adverse impact on populations of dung-dependent insects.

HOW SUPPLIED

Ivermectin Injection for Cattle and Swine is available in five ready-to-use pack sizes:

The 50 mL pack is a multiple-dose, rubber-capped bottle. Each bottle contains sufficient solution to treat 10 head of 550 lb (250 kg) cattle or 100 head of 38 lb (17.3 kg) swine.

The 100 mL pack is a multiple-dose, rubber-capped bottle. Each bottle contains sufficient solution to treat 20 head of 550 lb (250 kg) cattle or 200 head of 38 lb (17.3 kg) swine.

The 250 mL pack is a multiple-dose, rubber-capped bottle. Each bottle contains sufficient solution to treat 50 head of 550 lb (250 kg) cattle or 500 head of 38 lb (17.3 kg) swine.

The 500 mL pack is a multiple-dose, rubber-capped bottle designed for use with automatic syringe equipment. Each bottle contains sufficient solution to treat 100 head of 550 lb (250 kg) cattle or 1000 head of 38 lb (17.3 kg) swine.

The 1000 mL pack is a multiple-dose, rubber-capped bottle designed for use with automatic syringe equipment. Each bottle contains sufficient solution to treat 200 head of 550 lb (250 kg) cattle or 2000 head of 38 lb (17.3 kg) swine.

Restricted Drug - California. Use Only as Directed.

Approved by FDA under ANADA # 200-437 Made in the UK.

Manufactured by:
Norbrook Laboratories Limited, Newry, BT35 6PU, Co. Down, Northem Ireland

Manufactured for:
Durvet, Inc., Blue Springs, MO 64014
www.durvet.com

Rev 10/20 004215I01

Principal Display Panel - 500 mL Carton Label

NDC 30798-243-17

durvet
Ivermectin
(ivermectin)
INJECTION FOR CATTLE
AND SWINE

1% Sterile Solution

A Parasiticide for the
Treatment and Control of
Internal and External Parasites
of Cattle and Swine.

Approved by FDA under ANADA # 200-437

500 mL (16.91 fl oz)

Principal Display Panel - 500 mL Vial Label

NDC 30798-243-17

durvet
Ivermectin
(ivermectin)
INJECTION FOR CATTLE
AND SWINE

1% Sterile Solution

500 mL (16.91 fl oz)

Approved by FDA
under ANADA # 200-437